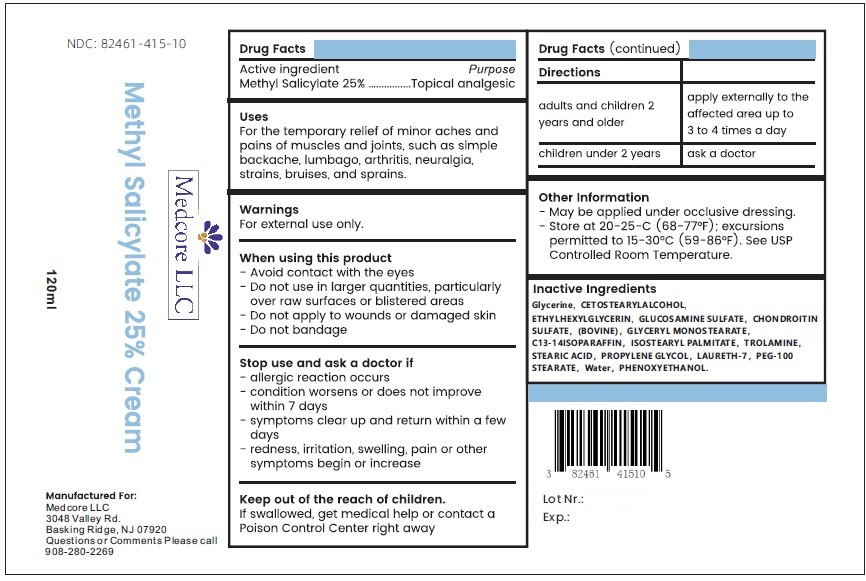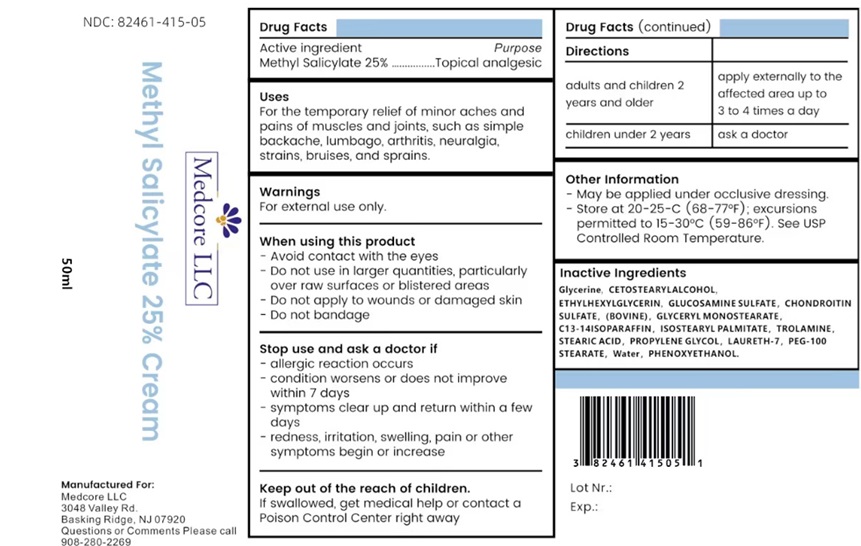 DRUG LABEL: Methyl Salicylate 25% Cream
NDC: 82461-415 | Form: CREAM
Manufacturer: Medcore LLC
Category: otc | Type: HUMAN OTC DRUG LABEL
Date: 20250714

ACTIVE INGREDIENTS: METHYL SALICYLATE 250 mg/1 mL
INACTIVE INGREDIENTS: GLYCERIN 60 mg/1 mL; CETOSTEARYL ALCOHOL 10 mg/1 mL; ETHYLHEXYLGLYCERIN 20 mg/1 mL; GLUCOSAMINE SULFATE 10 mg/1 mL; CHONDROITIN SULFATE (BOVINE) 5 mg/1 mL; GLYCERYL MONOSTEARATE 10 mg/1 mL; C13-14 ISOPARAFFIN 10 mg/1 mL; ISOSTEARYL PALMITATE 30 mg/1 mL; TROLAMINE 20 mg/1 mL; STEARIC ACID 30 mg/1 mL; PROPYLENE GLYCOL 50 mg/1 mL; LAURETH-7 30 mg/1 mL; PEG-100 MONOSTEARATE 50 mg/1 mL; WATER 410 mg/1 mL; PHENOXYETHANOL 5 mg/1 mL

Methyl Salicylate 25% Cream

Drug Facts

Active ingredient

Methyl Salicylate 25%

Purpose

Topical analgesic

Uses

For the temporary relief of minor aches and pains of muscles and joints, such as simple backache, lumbago, arthritis, neuralgia, strains, bruises, and sprains.

Warnings

For external use only.

When using this product

- Avoid contact with the eyes
- Do not use in larger quantities, particularly over raw surfaces or blistered areas
- Do not apply to wounds or damaged skin
- Do not bandage

Stop use and ask a doctor if

- allergic reaction occurs
- condition worsens or does not improve within 7 days
- symptoms clear up and return within a few days
- redness, irritation, swelling, pain or other symptoms begin or increase

Keep out of the reach of children.

If swallowed, get medical help or contact a Poison Control Center right away

Directions

adults and children 2 years and older | apply externally to the affected area up to 3 to 4 times a day
children under 2 years | ask a doctor

Other Information

- May be applied under occlusive dressing.
- Store at 20-25-C (68-77°F); excursions permitted to 15-30°C (59-86°F). See USP Controlled Room Temperature.

Inactive Ingredients

Glycerine, CETOSTEARYLALCOHOL, ETHYLHEXYLGLYCERIN, GLUCOSAMINE SULFATE, CHONDROITIN SULFATE, (BOVINE), GLYCERYL MONOSTEARATE, C13-14ISOPARAFFIN, ISOSTEARYL PALMITATE, TROLAMINE, STEARIC ACID, PROPYLENE GLYCOL, LAURETH-7, PEG-100 STEARATE, Water, PHENOXYETHANOL.

Manufactured For:
Medcore LLC
3048 Valley Rd.
Basking Ridge, NJ 07920
Questions or Comments Please call
908-280-2269

PRINCIPAL DISPLAY PANEL

NDC: 82461-415-10

Medcore LLC

Methyl Salicylate 25% Cream

120mL

Manufactured For:
Medcore LLC
3048 Valley Rd.
Basking Ridge, NJ 07920
Questions or Comments Please call
908-280-2269

PRINCIPAL DISPLAY PANEL

NDC: 82461-415-05

Medcore LLC

Methyl Salicylate 25% Cream

50mL

Manufactured For:
Medcore LLC
3048 Valley Rd.
Basking Ridge, NJ 07920
Questions or Comments Please call
908-280-2269